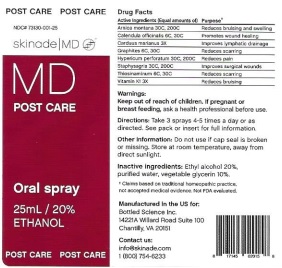 DRUG LABEL: MD Post Care
NDC: 73130-001 | Form: SPRAY
Manufacturer: Bottled Science, Inc.
Category: homeopathic | Type: HUMAN OTC DRUG LABEL
Date: 20210121

ACTIVE INGREDIENTS: ARNICA MONTANA 30 [hp_C]/25 mL; CALENDULA OFFICINALIS FLOWERING TOP 6 [hp_C]/25 mL; MILK THISTLE 3 [hp_X]/25 mL; GRAPHITE 6 [hp_C]/25 mL; HYPERICUM PERFORATUM 30 [hp_C]/25 mL; DELPHINIUM STAPHISAGRIA SEED 30 [hp_C]/25 mL; ALLYLTHIOUREA 6 [hp_C]/25 mL; PHYTONADIONE 3 [hp_X]/25 mL
INACTIVE INGREDIENTS: ALCOHOL; WATER; GLYCERIN

MD Post Care

Drug Facts

Active Ingredients (Equal amounts of) Purpose

Arnica montana 30C, 200C Reduces bruising and swelling

Calendula officinalis 6C, 30C Promotes would healing

Carduus marianus 3X Improves lymphatic drainage

Graphites 6C, 30C Reduces scarring

Hypericum perforatum 30C, 200C Reduces pain

Staphysagria 30C, 200C Improves surgical wounds

Thiosinaminum 6C, 30C Reduces scarring

Vitamin K1 3X Reduces bruising

† Claims based on traditional homeopathic practice,

not accepted medical evidence. Not FDA evaluated.

INDICATIONS AND USAGE

Reduces bruising and swelling

Promotes would healing

Improves lymphatic drainage

Reduces scarring

Reduces pain

Improves surgical wounds

Reduces scarring

Reduces bruising

Warnings:

Keep out of reach of children. If pregnant or

breast feeding, ask a health care professional before use.

Keep out of reach of children.

DOSAGE AND ADMINISTRATION

Directions: Take 3 sprays 4-5 times a day or as

directed. See pack or insert for full information.

Other information: Do not use if cap seal is broken

or missing. Store at room temperature, away from

direct sunlight.

Inactive ingredients: Ethyl alcohol 20%,

purified water, vegetable glycerin 10%

QUESTIONS

Manufactured In the US for:

Bottled Science Inc.

14221A Willard Road Suite 100

Chantilly, VA 20151

Contact us:

info@skinade.com

1 (800) 754-6233

PACKAGE LABEL

POST CARE POST CARE

NDC# 73130-001-25

skinade ι MD

MD

POST CARE

Oral spray

25mL / 20%

ETHANOL

POST CARE POST CARE

PURPOSE

Reduces bruising and swelling

Promotes would healing

Improves lymphatic drainage

Reduces scarring

Reduces pain

Improves surgical wounds

Reduces scarring

Reduces bruising